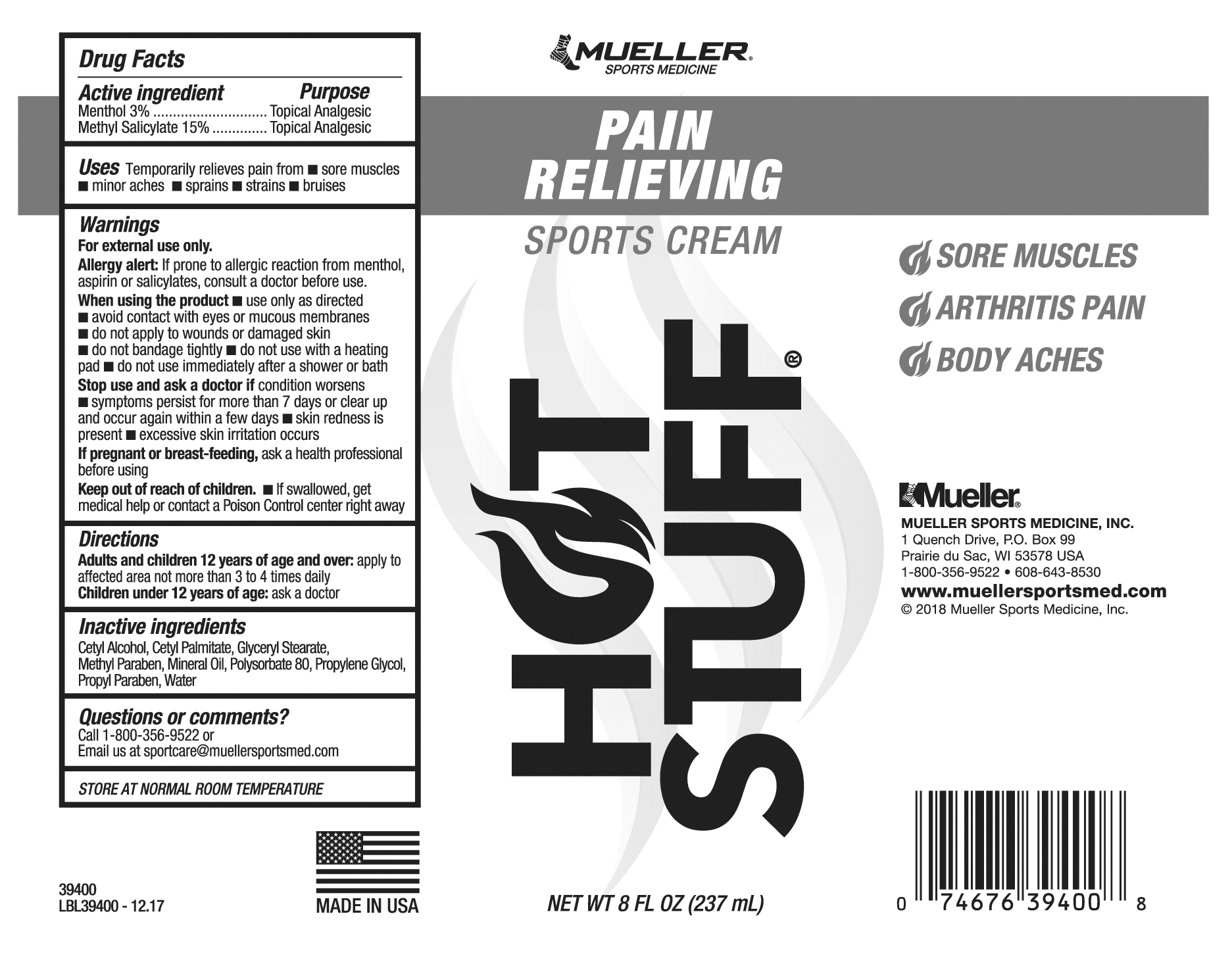 DRUG LABEL: Hot Stuff
NDC: 52564-108 | Form: CREAM
Manufacturer: Mueller Sports Medicine
Category: otc | Type: HUMAN OTC DRUG LABEL
Date: 20190422

ACTIVE INGREDIENTS: MENTHOL 0.03 g/1 g; METHYL SALICYLATE 0.15 g/1 g
INACTIVE INGREDIENTS: MINERAL OIL; PROPYLENE GLYCOL; CETYL ALCOHOL; CETYL PALMITATE; GLYCERYL MONOSTEARATE; METHYLPARABEN; POLYSORBATE 80; PROPYLPARABEN; WATER

Active Ingredients

Menthol 3%

Methyl Salicylate 15%

Pupose

Purpose

Topical Analgesic

Topical Analgesic

Uses

Temporarily relieves pain from

- sore muscles
- minor aches
- sprains
- strains
- bruises

WARNINGS

For external use only

Allergy alert: If prone to allergic reaction from menthol, aspirin or salicylates, consult a doctor before use.

When using this product

- use only as directed
- avoid contact with eyes or mucous membranes
- do not apply to wounds or damaged skin
- do not bandage tightly
- do not use with a heating pad
- do not use immediately after a shower or bath

Stop use and ask a doctor if condition worsens

- symptoms persist for more than 7 days or clear up and occur again within a few days
- skin redness is present
- excessive skin irritation occurs

If pregnant or breast-feeding, ask a health professional before using

Keep out of reach of children

Keep out of children

- if swallowed, get medical help or contact a Poison Control center right away

Directions

Adults and children 12 years of age and over: apply to affected area not more than 3 to 4 times daily

Children under 12 years of age: ask a doctor

Inactive ingredients

Cetyl Alcohol, Cetyl Palmitate, Glyceryl Stearate, Methyl Paraben, Mineral Oil, Polysorbate 80, Propylene Glycol, Propyl Paraben, Water

Questions or comments?

Call 1-800-356-9522 or

Email us at sportcare@muellersportsmed.com

OTHER SAFETY INFORMATION

STORE AT NORMAL ROOM TEMPERATURE